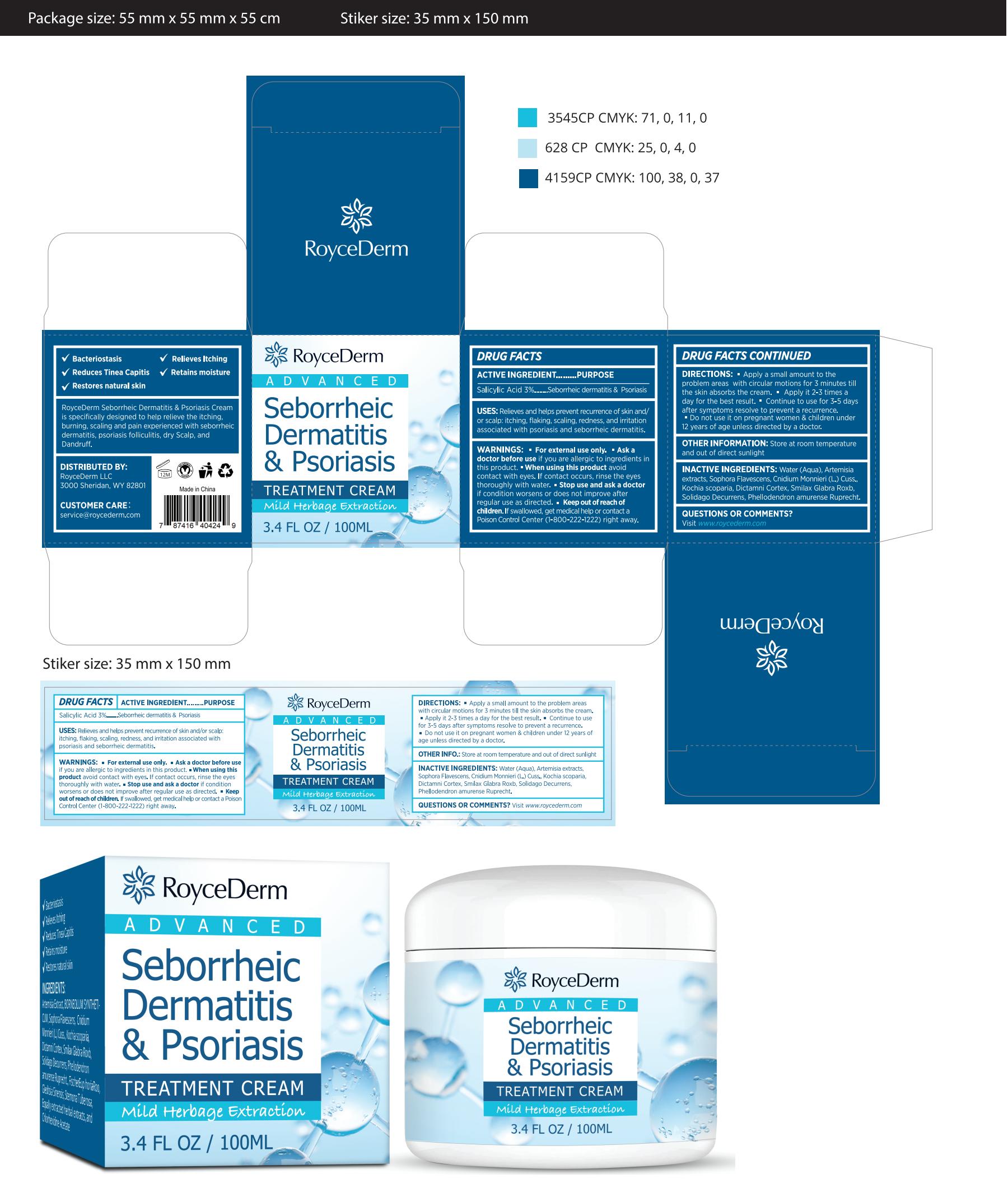 DRUG LABEL: Roycederm Seborrheic Dermatitis Psoriasis Cream
NDC: 84746-001 | Form: CREAM
Manufacturer: Shandong Yuyaotang Pharmaceutical Co., Ltd
Category: otc | Type: HUMAN OTC DRUG LABEL
Date: 20241017

ACTIVE INGREDIENTS: SALICYLIC ACID 3 g/100 mL
INACTIVE INGREDIENTS: SMILAX GLABRA WHOLE; SOPHORA FLAVESCENS WHOLE; WATER; ARTEMISIA ARGYI LEAF; CNIDIUM MONNIERI WHOLE; DICTAMNUS DASYCARPUS ROOT; PHELLODENDRON AMURENSE WHOLE; SOLIDAGO DECURRENS WHOLE

84746-001 Update

Active Ingredient

Salicylic Acid 3%

Purpose

Seborrheic dermatitis & Psoriasis

Use

Relieves and helps prevent recurrence of skin and/or scalp: itching, flaking, scaling, redness, and irritationassociated with psoriasis and seborrheic dermatitis.

Warnings

"Forexternaluse only. " Ask adoctor before use if you are allergic to ingredients inthis product, " When using this product avoid
contact with eyes.lf contact occurs, rinse the eyesthoroughly with water. " Stop use and ask a doctorif condition worsens or does not improve afterreqular use as directed.. Keep out ofreach ofchildren. lf swallowed, get medical help or contact aPoison Control Center (1-800-222-1222) right away.

Do not use it on pregnant women & children under12 years of age unless directed by a doctor.

When Using

Forexternaluse only.

Stop Use

When using this product avoid
contact with eyes.lf contact occurs, rinse the eyesthoroughly with water. " Stop use and ask a doctorif condition worsens or does not improve afterreqular use as directed.

Ask Doctor

Ask adoctor before use if you are allergic to ingredients inthis product

Keep Oot Of Reach Of Children

Keep out ofreach ofchildren

Directions

Apply a small amount to theproblem areas with circular motions for 3 minutes tillthe skin absorbs the cream." Apply it 2-3 times aday for the best result. " Continue to use for 3-5 daysafter symptoms resolve to prevent a recurrence.Do not use it on pregnant women & children under12 years of age unless directed by a doctor.

Other information

Store at room temperatureand out of direct sunlight

Inactive ingredients

Water (Aqua), Artemisiaextracts, Sophora Flavescens, Cnidium Monnieri (L.)CussKochia scoparia, Dictamni Cortex, Smilax Glabra Roxb,Solidago Decurrens, Phellodendron amurense Ruprecht,

Questions

Visit www.roycederm.com